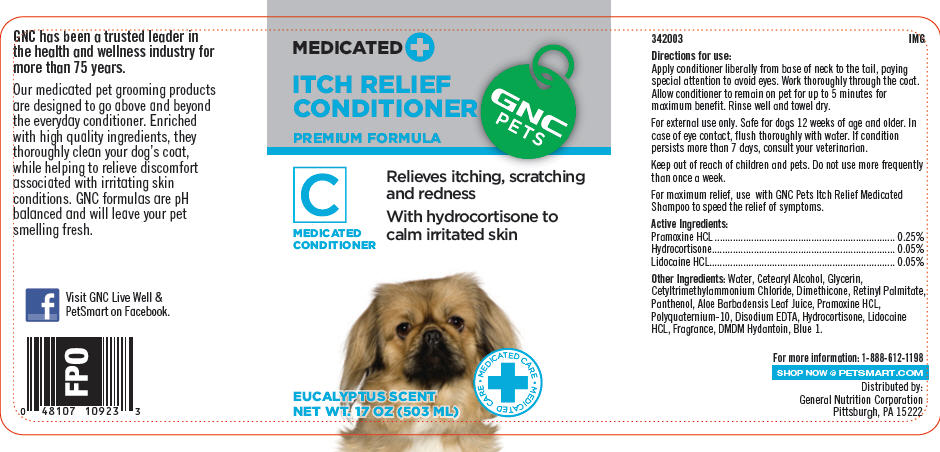 DRUG LABEL: GNC Pets Itch Relief Conditioner (Premium Formula)
NDC: 43655-003 | Form: SHAMPOO
Manufacturer: General Nutrition Corporation
Category: animal | Type: OTC ANIMAL DRUG LABEL
Date: 20181105

ACTIVE INGREDIENTS: Pramoxine Hydrochloride 2.5 mg/1 mL; Hydrocortisone 0.5 mg/1 mL; Lidocaine Hydrochloride 0.5 mg/1 mL
INACTIVE INGREDIENTS: Water; Cetostearyl Alcohol; Glycerin; Cetrimonium Chloride; Dimethicone; Vitamin A Palmitate; Panthenol; Aloe Vera Leaf; Polyquaternium-10 (400 MPA.S at 2%); Edetate Disodium; DMDM Hydantoin; Fd&C Blue No. 1

GNC Pets Itch Relief Conditioner (Premium Formula)

342003
IMG

DOSAGE AND ADMINISTRATION

Directions for use:

Apply conditioner liberally from base of neck to the tail, paying special attention to avoid eyes. Work thoroughly through the coat. Allow conditioner to remain on pet for up to 5 minutes for maximum benefit. Rinse well and towel dry.

SAFE HANDLING WARNING

For external use only. Safe for dogs 12 weeks of age and older. In case of eye contact, flush thoroughly with water. If condition persists more than 7 days, consult your veterinarian.

Keep out of reach of children and pets. Do not use more frequently than once a week.

For maximum relief, use with GNC Pets Itch Relief Medicated Shampoo to speed the relief of symptoms.

DESCRIPTION

Active Ingredients:
Pramoxine HCL | 0.25%
Hydrocortisone | 0.05%
Lidocaine HCL | 0.05%

Other Ingredients: Water, Cetearyl Alcohol, Glycerin, Cetyltrimethylammonium Chloride, Dimethicone, Retinyl Palmitate, Panthenol, Aloe Barbadensis Leaf Juice, Pramoxine HCL, Polyquaternium-10, Disodium EDTA, Hydrocortisone, Lidocaine HCL, Fragrance, DMDM Hydantoin, Blue 1.

For more information: 1-888-612-1198

SHOP NOW @ PETSMART.COM

Distributed by:
General Nutrition Corporation
Pittsburgh, PA 15222

PRINCIPAL DISPLAY PANEL - 503 ML Bottle Label

MEDICATED +
ITCH RELIEF
CONDITIONER

PREMIUM FORMULA

GNC
PETS

C
MEDICATED
CONDITIONER

Relieves itching, scratching
and redness

With hydrocortisone to
calm irritated skin

• MEDICATED CARE
+
• MEDICATED CARE

EUCALYPTUS SCENT
NET WT. 17 OZ (503 ML)